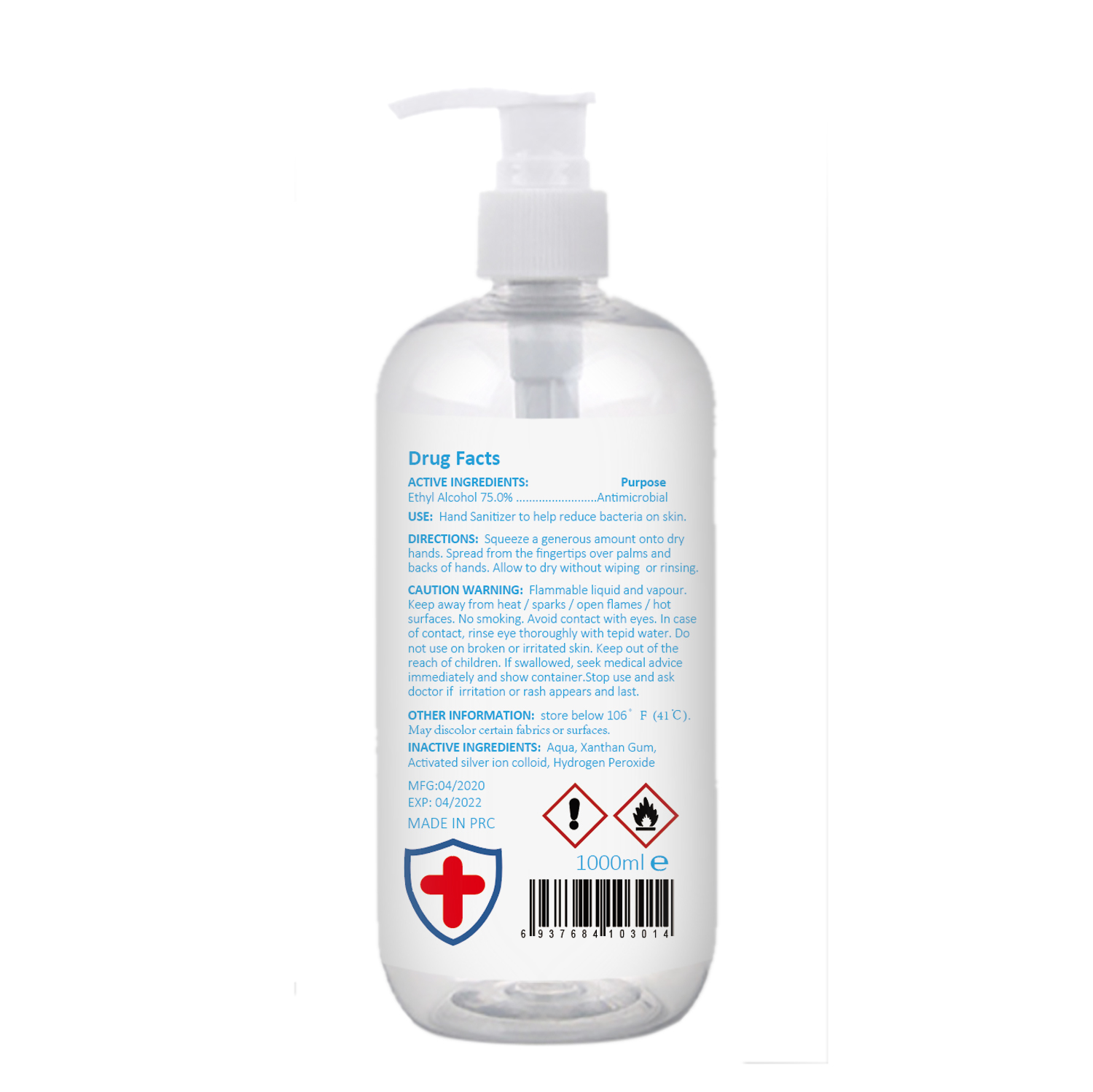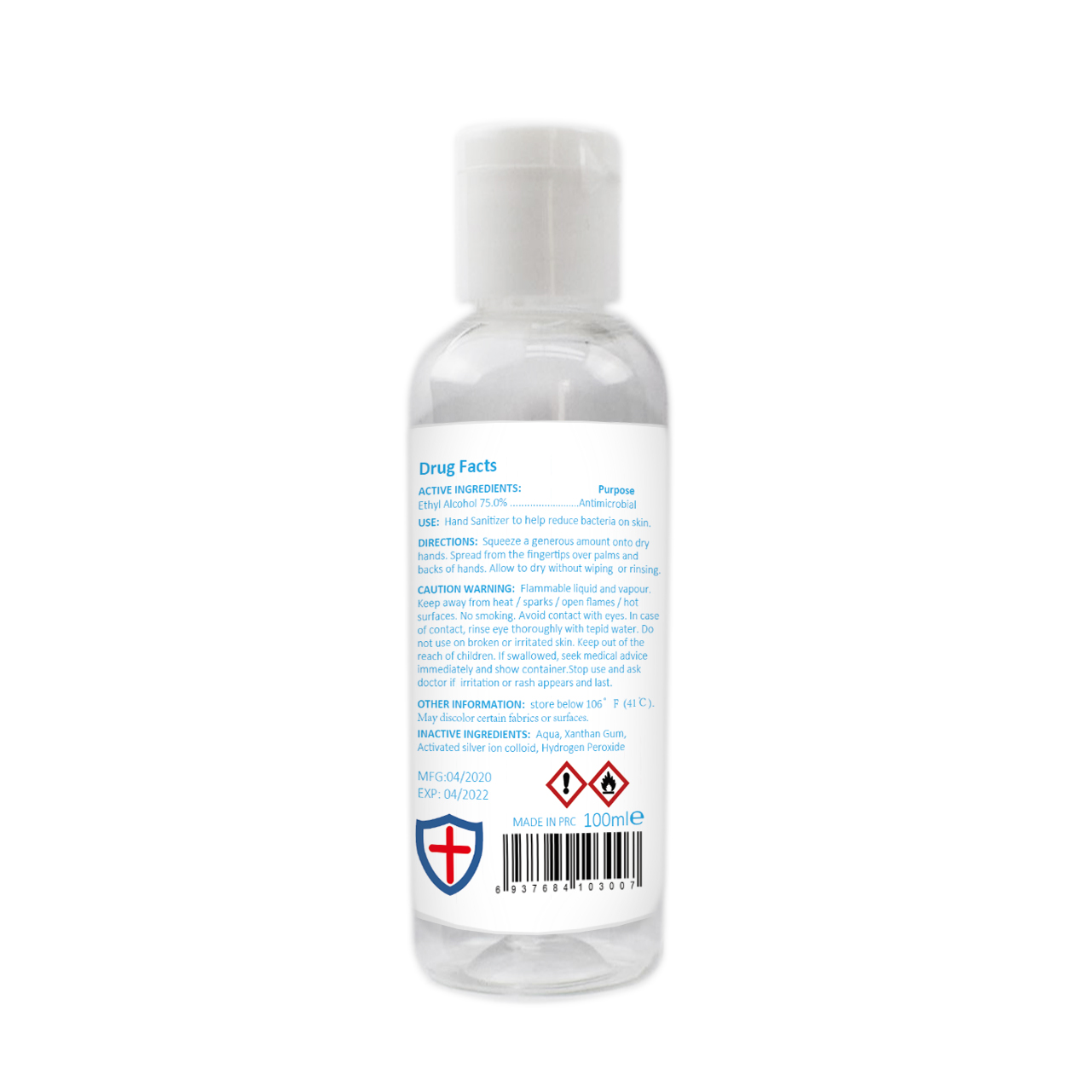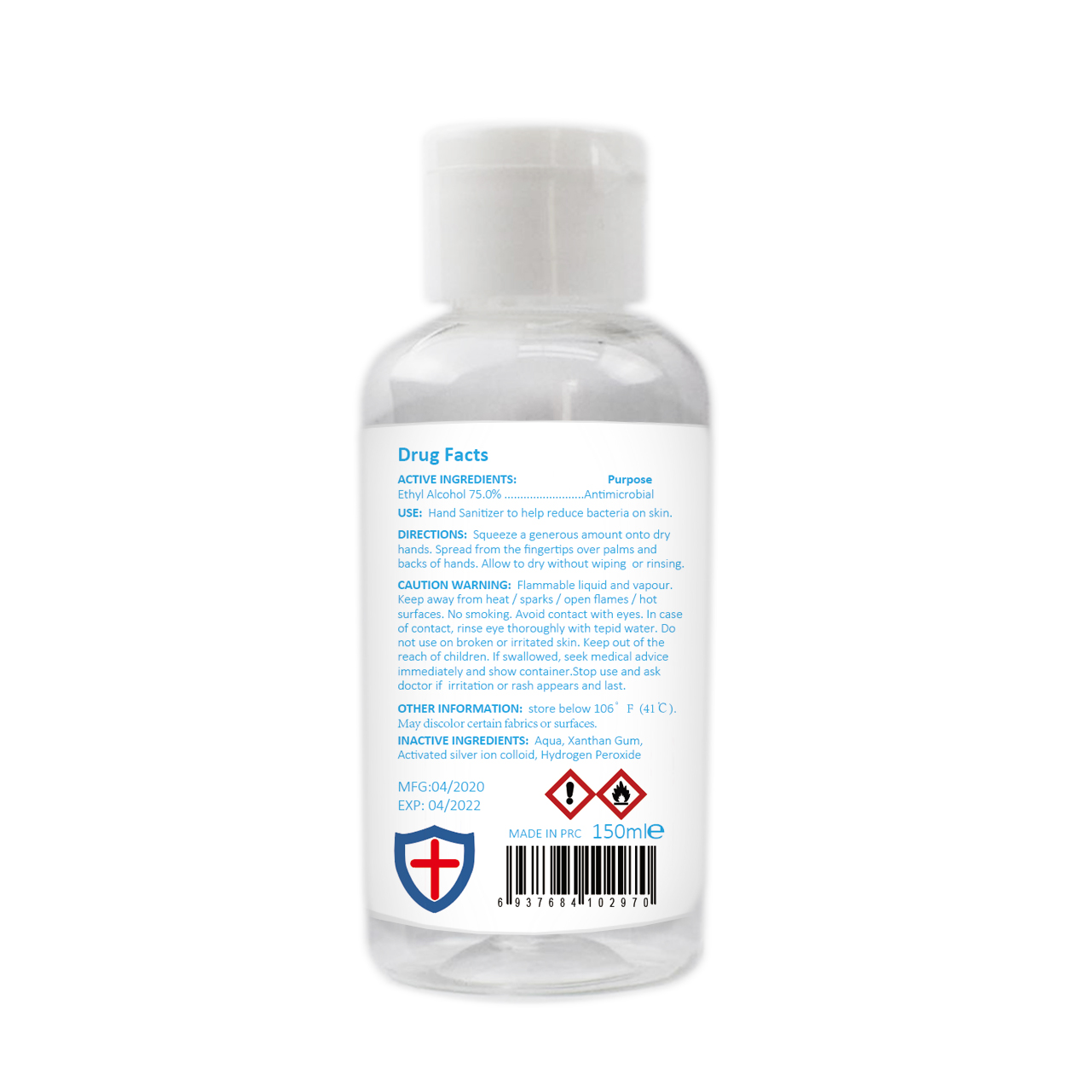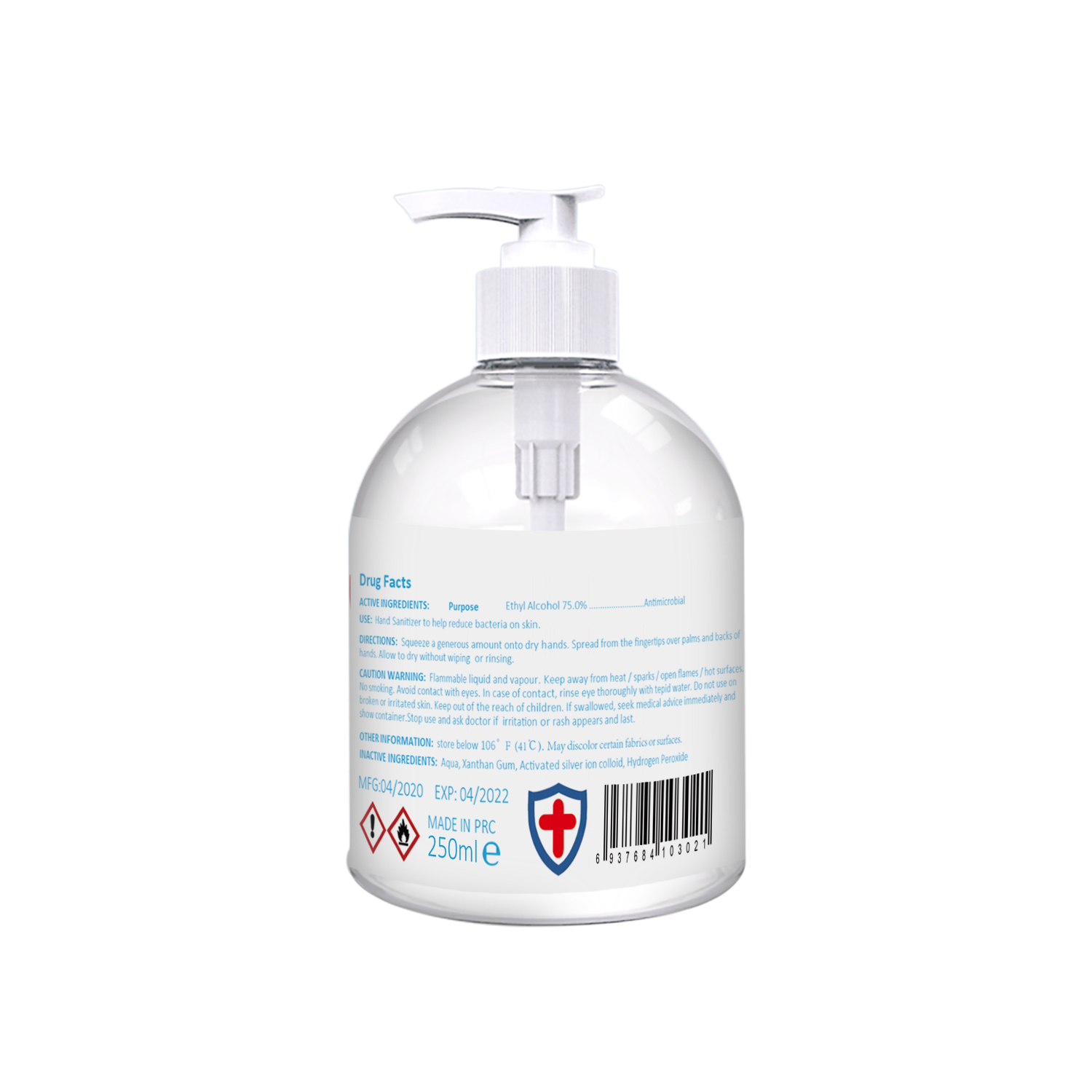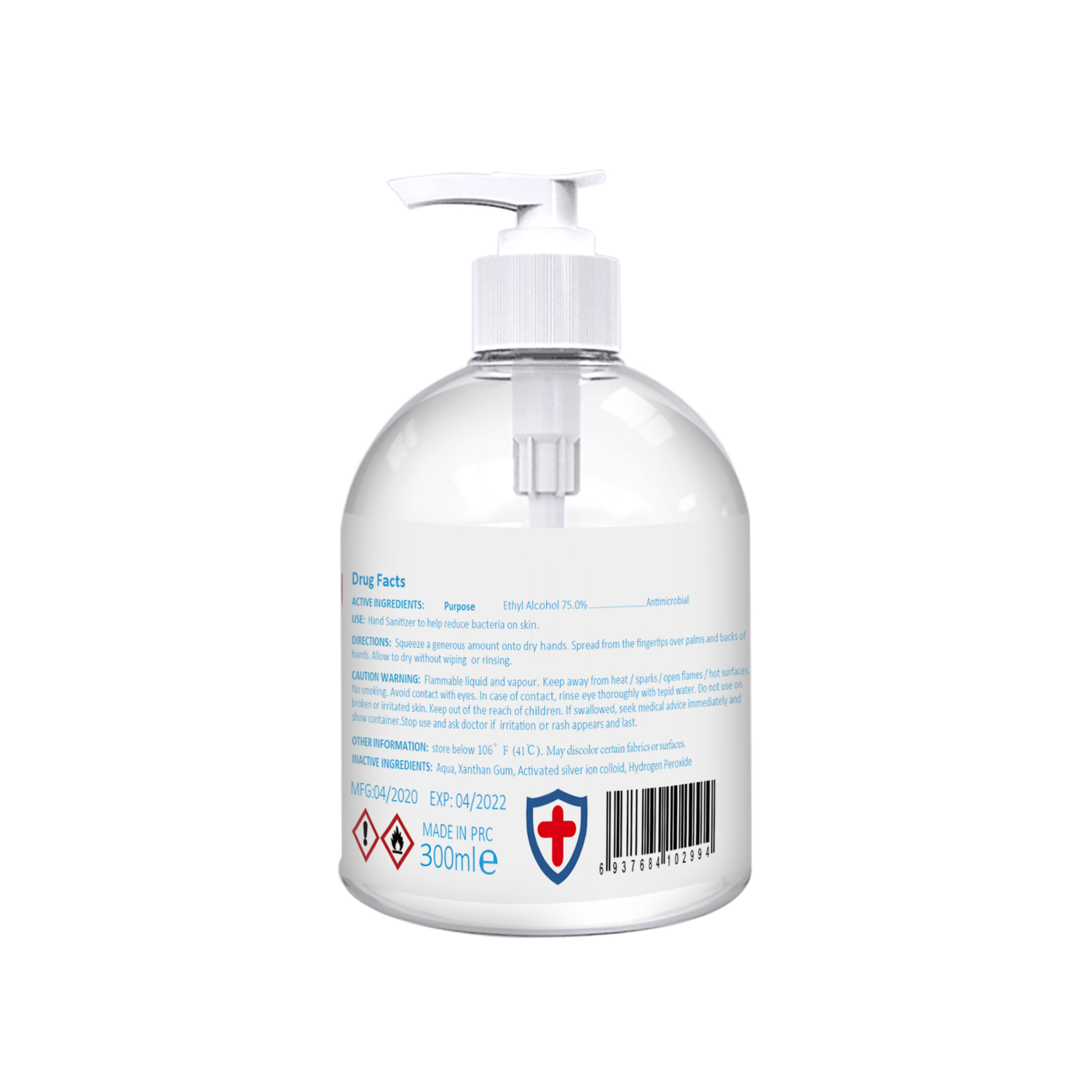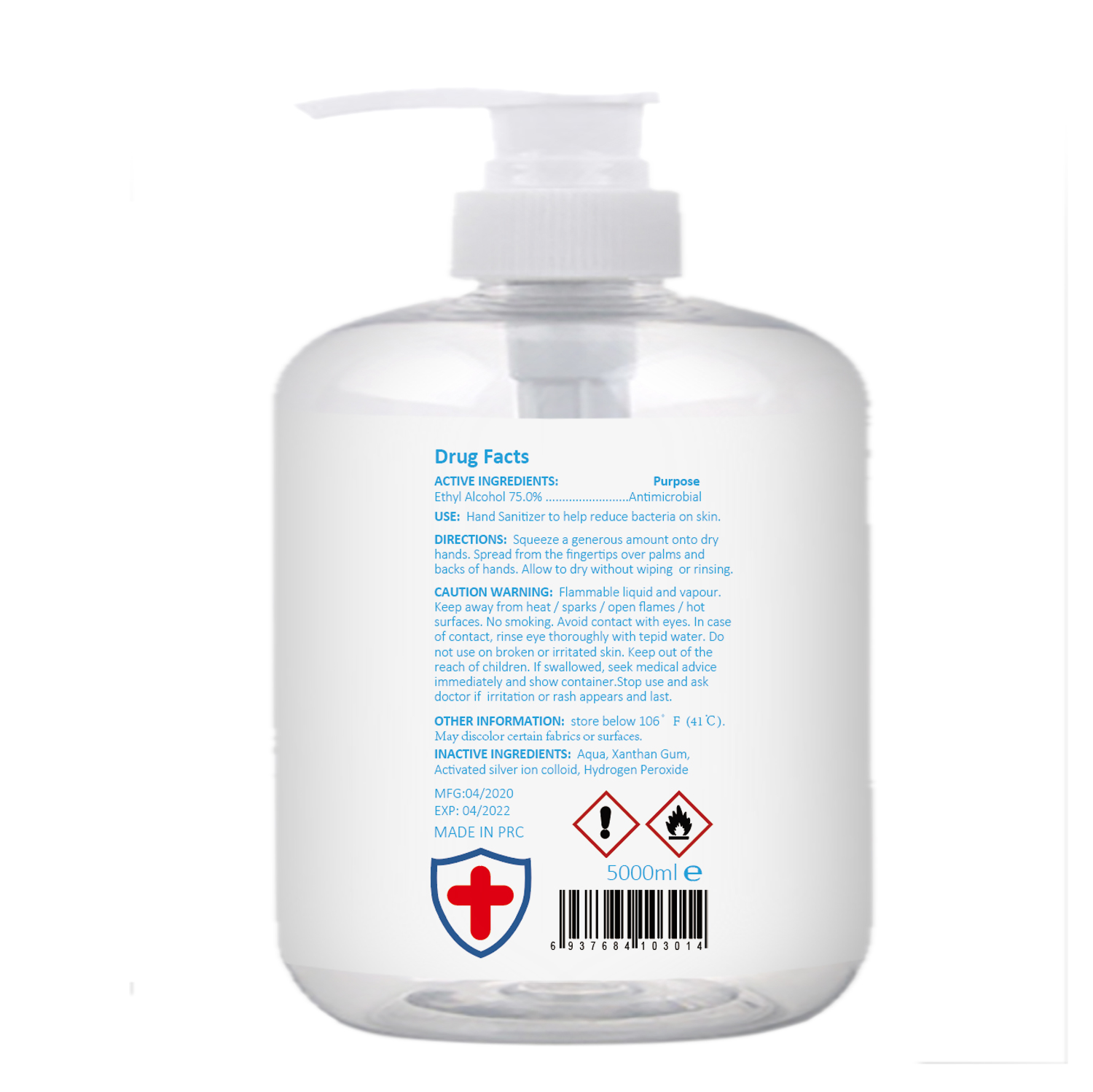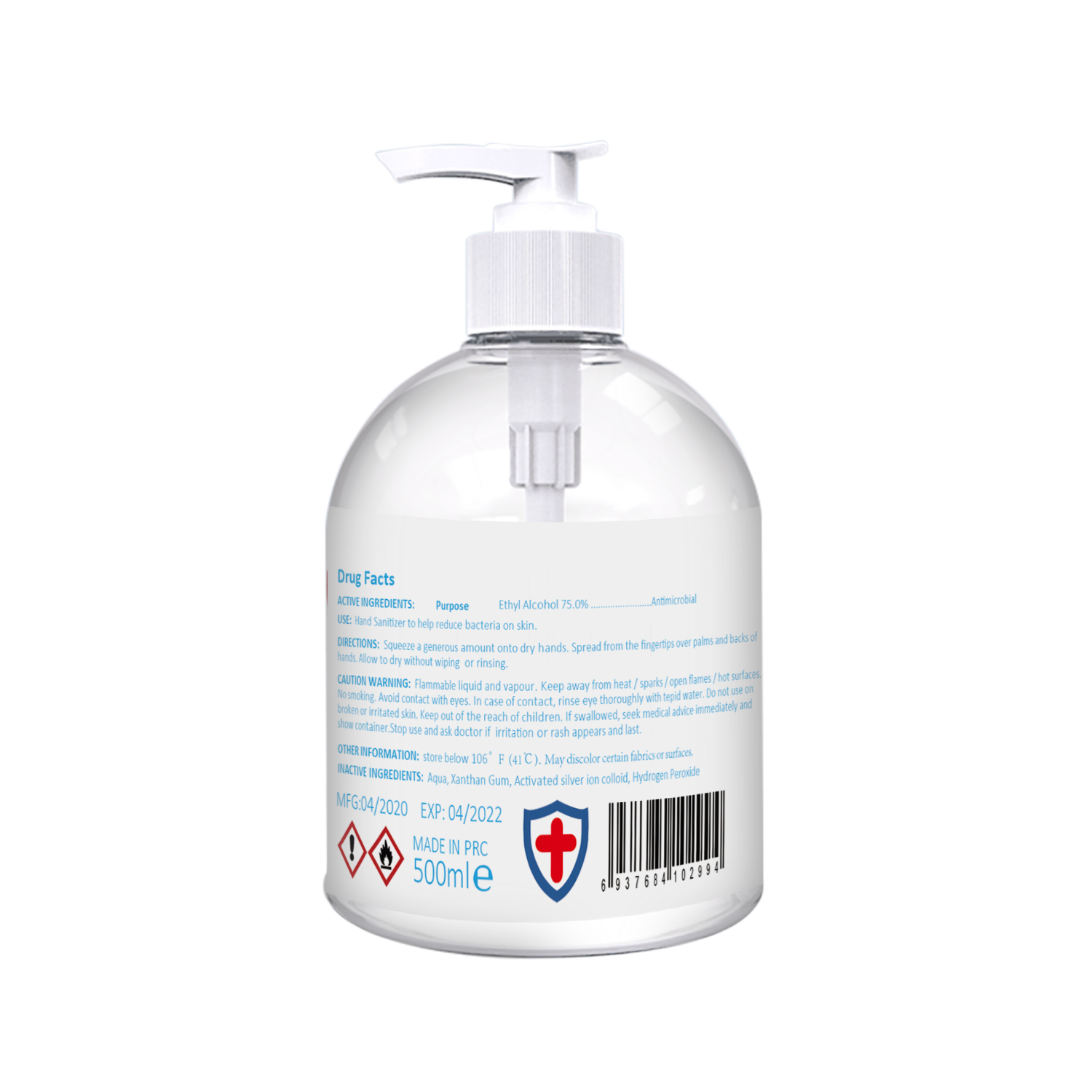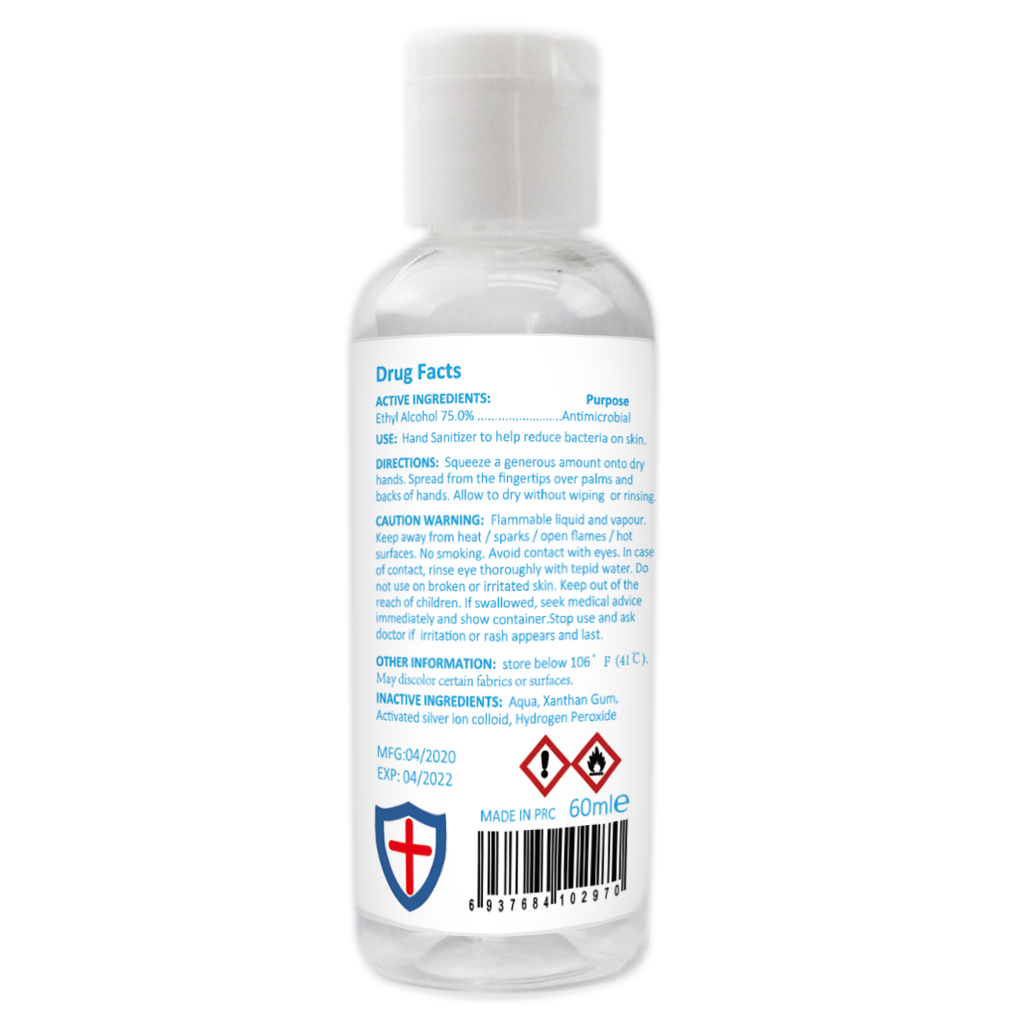 DRUG LABEL: Hand Sanitizer
NDC: 75605-005 | Form: GEL
Manufacturer: Guangzhou Shiruoni Cosmetics Co.,Ltd
Category: otc | Type: HUMAN OTC DRUG LABEL
Date: 20200420

ACTIVE INGREDIENTS: ALCOHOL 75 mL/100 mL
INACTIVE INGREDIENTS: SILVER; XANTHAN GUM; HYDROGEN PEROXIDE; WATER

Hand Sanitizer

Active Ingredient(s)

Alcohol 75% v/v. Purpose: Antiseptic

Purpose

Antiseptic, Hand Sanitizer

Use

Hand Sanitizer to help reduce bacteria on skin

Directions

Squeeze a generous amount onto dry hands Spread from the fingertips over palms and backs of hands. Allow to dry without wiping or rinsing

CAUTION WARNING

Flammable liquid and vapour. Keep away from heat/sparks/open flames/ hot surfaces. No smoking. Avoid contact with eyes. In case of contact, rinse eye thoroughly with tepid water. Do not use on broken or irritated skin. Keep out of the reach of children. If swallowed, seek medical advice immediately and show container.Stop use and ask doctor if irritation or rash appears and last

Other information

store below 106 F(41 C)

May discolor certain fabrics or surfaces

Inactive ingredients

Aqua, Xanthan Gum, Activated silver ion colloid, Hydrogen Peroxide